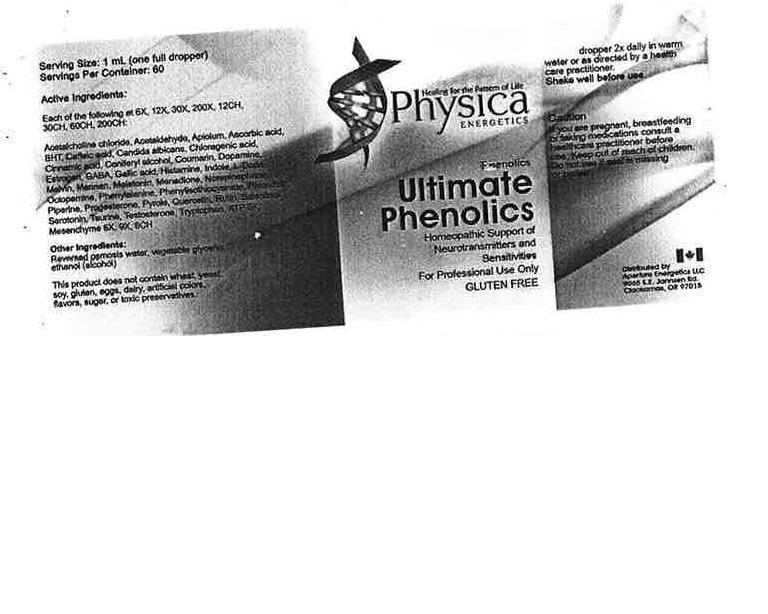 DRUG LABEL: Ultimate Phenolics
NDC: 54118-7017 | Form: SOLUTION/ DROPS
Manufacturer: ABCO Labratories, Inc.
Category: homeopathic | Type: HUMAN OTC DRUG LABEL
Date: 20150716

ACTIVE INGREDIENTS: ACETYLCHOLINE CHLORIDE 6 [hp_X]/60 mL; ACETALDEHYDE 6 [hp_X]/60 mL; PARSLEY 6 [hp_X]/60 mL; ASCORBIC ACID 6 [hp_X]/60 mL; BUTYLATED HYDROXYTOLUENE 6 [hp_X]/60 mL; CAFFEIC ACID 6 [hp_X]/60 mL; CANDIDA ALBICANS 6 [hp_X]/60 mL; CHLOROGENIC ACID 6 [hp_X]/60 mL; CINNAMIC ACID 6 [hp_X]/60 mL; CONIFERYL ALCOHOL 6 [hp_X]/60 mL; COUMARIN 6 [hp_X]/60 mL; DOPAMINE 6 [hp_X]/60 mL; ESTROGENS, CONJUGATED 6 [hp_X]/60 mL; .GAMMA.-AMINOBUTYRIC ACID 6 [hp_X]/60 mL; GALLIC ACID 6 [hp_X]/60 mL; HISTAMINE 6 [hp_X]/60 mL; INDOLE 6 [hp_X]/60 mL; DOPA, DL- 6 [hp_X]/60 mL; MALVIN 6 [hp_X]/60 mL; YEAST MANNAN 6 [hp_X]/60 mL; MELATONIN 6 [hp_X]/60 mL; MENADIONE 6 [hp_X]/60 mL; NORADRENALINE, (+/-)- 6 [hp_X]/60 mL; OCTOPAMINE 6 [hp_X]/60 mL; PHENYLALANINE 6 [hp_X]/60 mL; PHENYL ISOTHIOCYANATE 6 [hp_X]/60 mL; PHLORIZIN 6 [hp_X]/60 mL; PIPERINE 6 [hp_X]/60 mL; PROGESTERONE 6 [hp_X]/60 mL; PYRROLE 6 [hp_X]/60 mL; QUERCETIN 6 [hp_X]/60 mL; RUTIN 6 [hp_X]/60 mL; SALSOLINOL 6 [hp_X]/60 mL; SEROTONIN 6 [hp_X]/60 mL; TAURINE 6 [hp_X]/60 mL; TESTOSTERONE 6 [hp_X]/60 mL; TRYPTOPHAN 6 [hp_X]/60 mL; ADENOSINE TRIPHOSPHATE 6 [hp_X]/60 mL; BOS TAURUS MESENCEPHALON 6 [hp_X]/60 mL
INACTIVE INGREDIENTS: WATER; ALCOHOL; GLYCERIN

Ultimate Phenolics

WARNINGS

- If you are pregnant, breastfeeding or taking medications consult a healthcare practitioner before use.
- Keep out of reach of children.
- Do not use if seal is missing or broken.

KEEP OUT OF REACH OF CHILDREN!

DOSAGE AND ADMINISTRATION

- One full dropper 2x daily in water or as directed by a health care practitioner.
- Shake well.

PURPOSE

Homeopathic Support of Neurotransmitter and Sensitivities.

INDICATIONS AND USAGE

Phenolics

INACTIVE INGREDIENT

Water: Reverse osmosis, Ethyl Alcohol : Grain : 190 proof, Glycerine.

ACTIVE INGREDIENT

Each of the following at 6X, 12X, 30X, 200X, 12CH, 30CH, 60CH, 200CH.

Acetalcholine chloride Combo, Acetaldehyde Combo, Apiolum Combo, Ascorbic Aid Combo, Apiolum Combo, Ascorbic Acid Combo, BHT Combo, Caffeic acid Combo, Candida albicans Combo, Chloragenic acid Combo, Cinnamic acid Combo, Coniferyl alcohol Combo, Coumarin Combo, Dopamin Combo, Estrogen Combo, GABA Combo, Gallic acid Combo, Histamine Combo, Indole Combo, L-Dopa Combo, Malvin Combo, Mannan Combo, Melatonin Combo, Menadione Combo, Noepinephrine Combo, Octopamine Combo, Phenylalanine Combo, Phenylisothiocyanate Combo, Phloridzin Combo, Piperin Combo, Progesterone Combo, Pyrole Combo, Quercetin Combo, Rutin Combo, Salsolinol Combo, Serotonin Combo, Taurine Combo, Testosterone Combo, Tryptophan Combo, ATP 5X, Mesenchyme 6X, 9X, 6C.